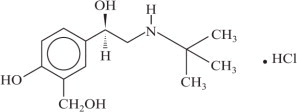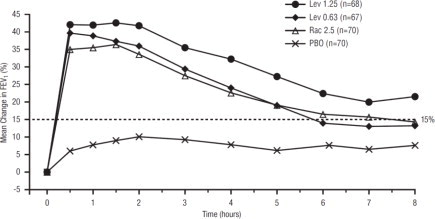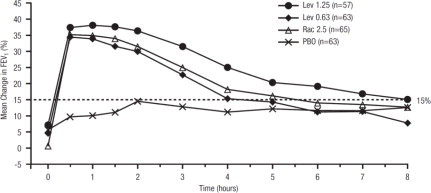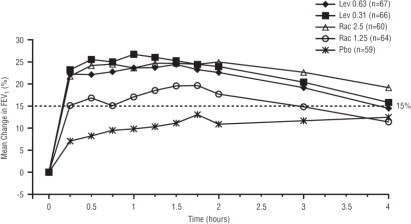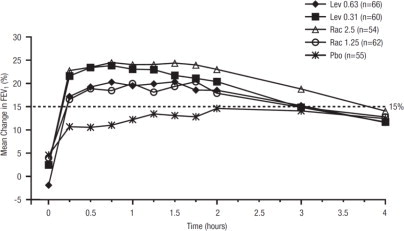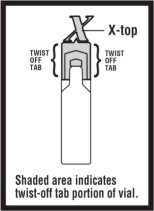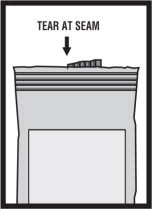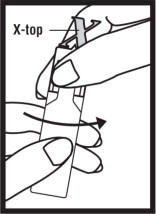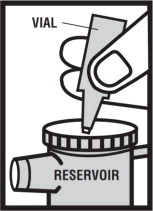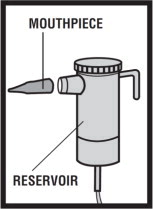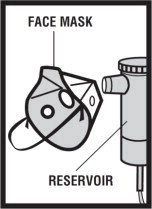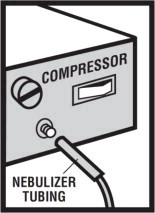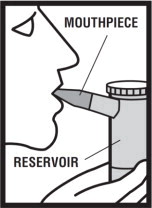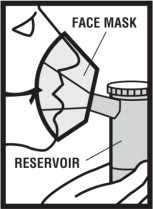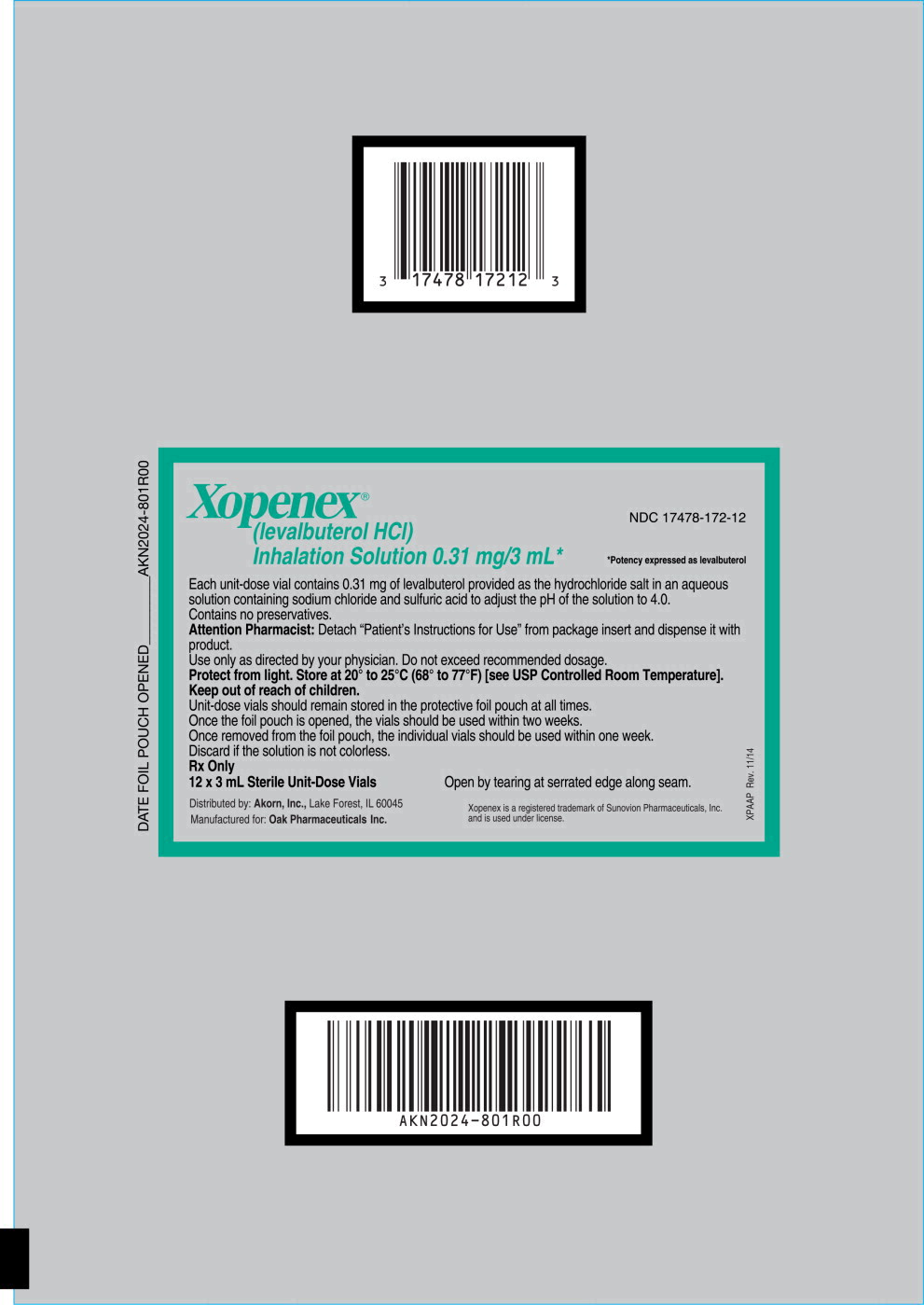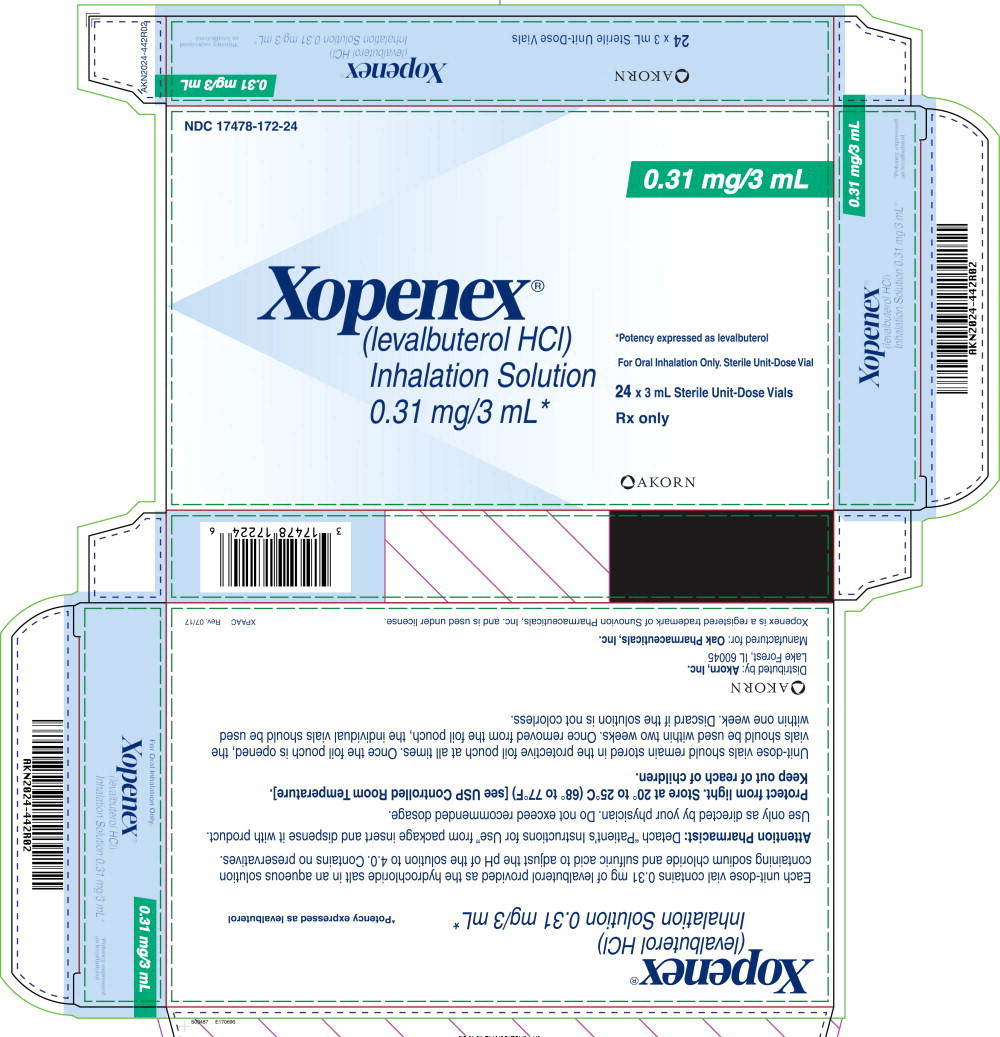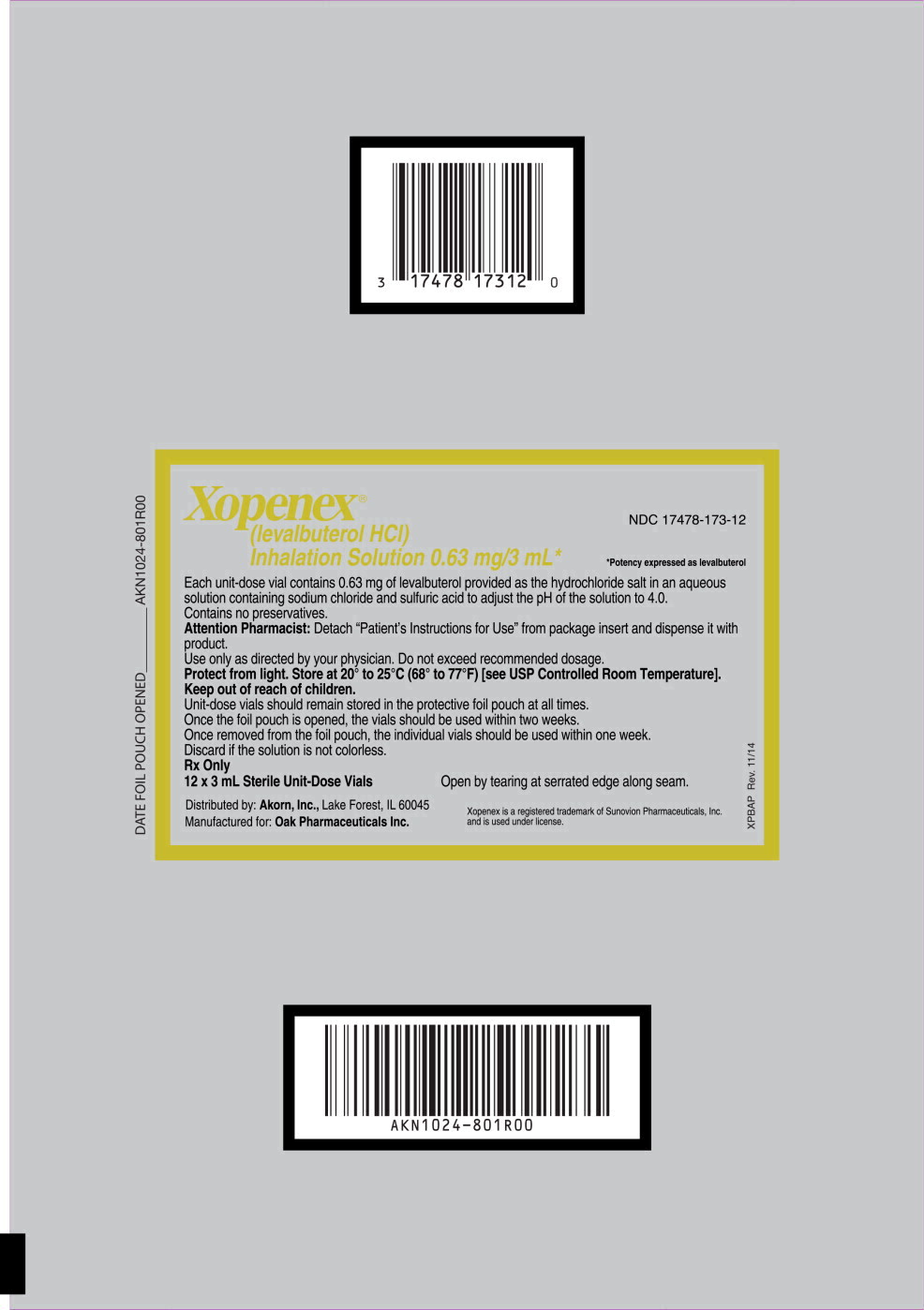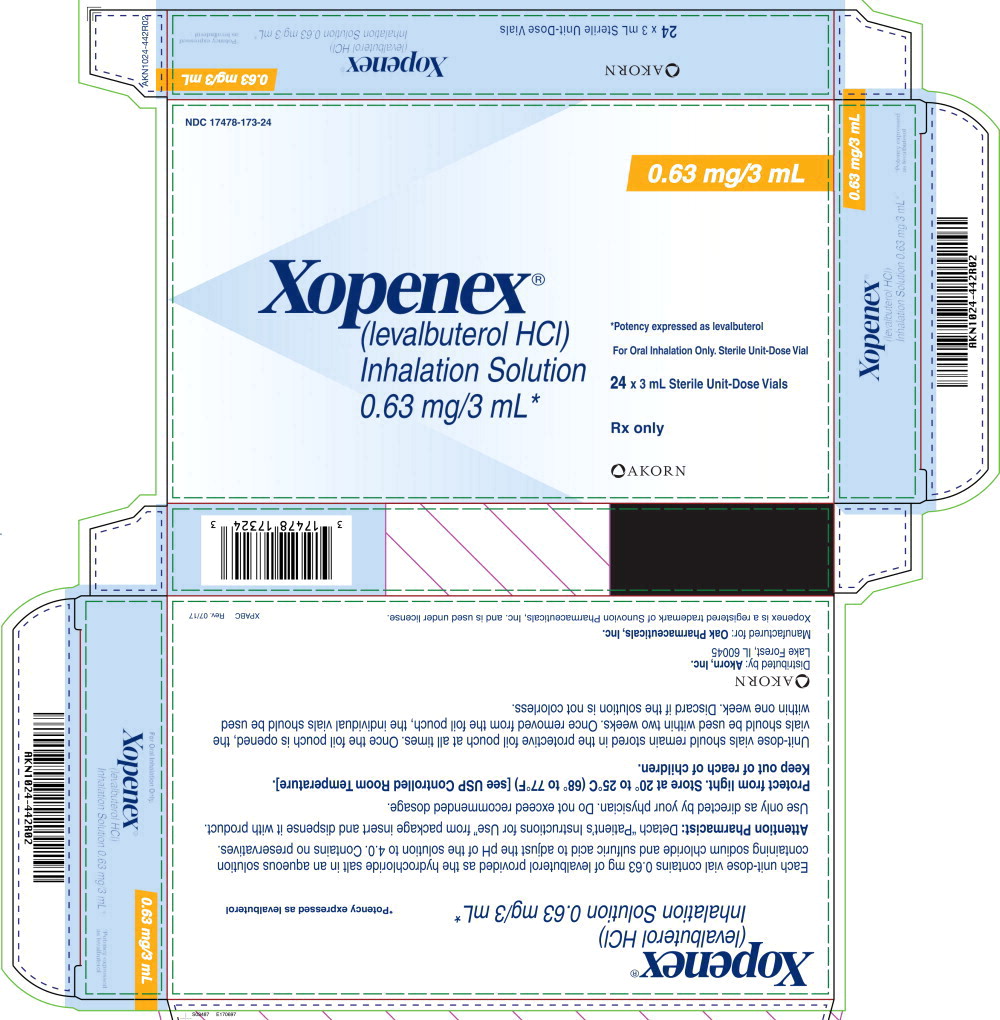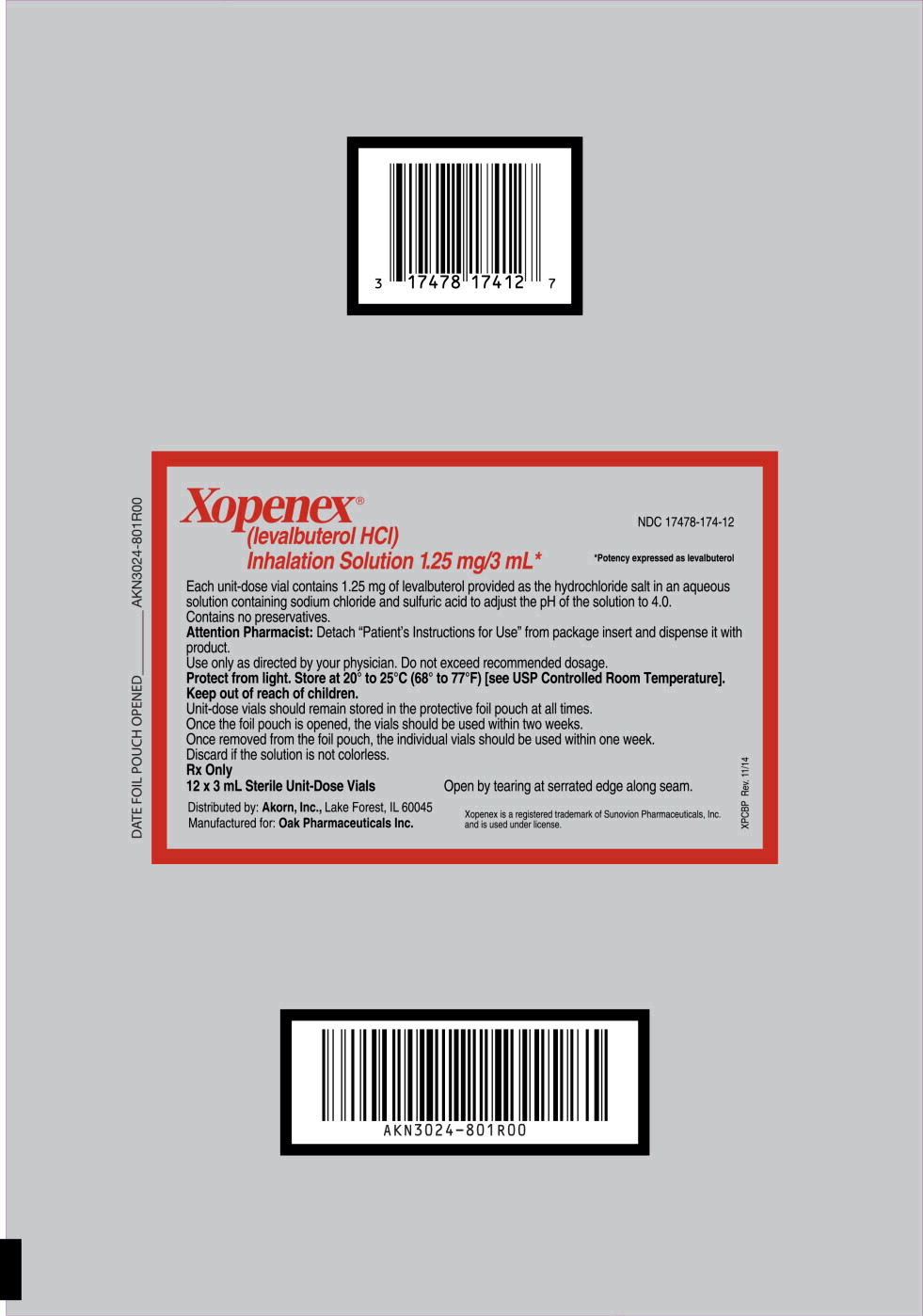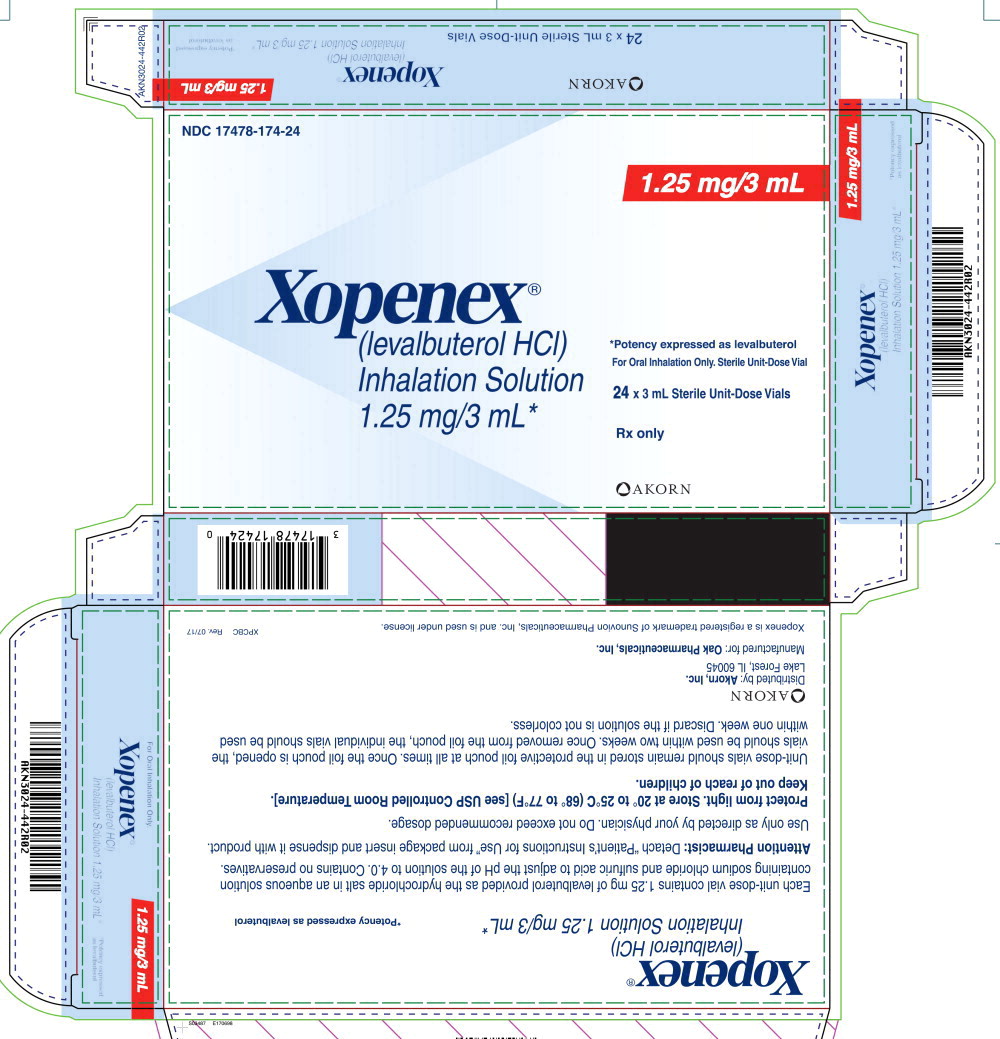 DRUG LABEL: Xopenex

NDC: 17478-172 | Form: SOLUTION
Manufacturer: Akorn
Category: prescription | Type: HUMAN PRESCRIPTION DRUG LABEL
Date: 20220914

ACTIVE INGREDIENTS: Levalbuterol Hydrochloride
 0.31 mg/3 mL
INACTIVE INGREDIENTS: Sodium Chloride; Sulfuric Acid; Water; Nitrogen

HIGHLIGHTS OF PRESCRIBING INFORMATION

These highlights do not include all the information needed to use XOPENEX® Inhalation Solution safely and effectively. See full prescribing information for XOPENEX® Inhalation Solution.
XOPENEX® (levalbuterol hydrochloride) Inhalation Solution
Initial U.S. Approval: 1999

1 INDICATIONS AND USAGE

XOPENEX (levalbuterol hydrochloride) Inhalation Solution is a beta2-adrenergic agonist indicated for:

- Treatment or prevention of bronchospasm in adults, adolescents, and children 6 years of age and older with reversible obstructive airway disease. (1)

2 DOSAGE AND ADMINISTRATION

- FOR ORAL INHALATION ONLY (2)
- Children 6 to 11 years old: 0.31 mg administered three times a day, by nebulization. Routine dosing should not exceed 0.63 mg three times a day. (2)
- Adults and Adolescents ≥12 years old: 0.63 mg administered three times a day, every 6 to 8 hours, by nebulization. The maximum recommended dose is 1.25 mg three times a day. (2)
- For use with a standard jet nebulizer (with a face mask or mouthpiece) connected to an air compressor. (2)

3 DOSAGE FORMS AND STRENGTHS

Inhalation Solution (unit-dose vial for nebulization): 0.31 mg/3 mL, 0.63 mg/3 mL and 1.25 mg/3 mL. (3)

4 CONTRAINDICATIONS

- Hypersensitivity to levalbuterol or racemic albuterol. (4)

5 WARNINGS AND PRECAUTIONS

- Life-threatening paradoxical bronchospasm may occur. Discontinue XOPENEX Inhalation Solution immediately and treat with alternative therapy. (5.1)
- Need for more doses of XOPENEX Inhalation Solution than usual may be a sign of deterioration of asthma and requires reevaluation of treatment. (5.2)
- XOPENEX Inhalation Solution is not a substitute for corticosteroids. (5.3)
- Cardiovascular effects may occur. Consider discontinuation of XOPENEX Inhalation Solution if these effects occur. Use with caution in patients with underlying cardiovascular disorders. (5.4)
- Excessive use may be fatal. Do not exceed recommended dose. (5.5)
- Immediate hypersensitivity reactions may occur. Discontinue XOPENEX Inhalation Solution immediately. (5.6)
- Hypokalemia and changes in blood glucose may occur. (5.7, 5.8)

6 ADVERSE REACTIONS

Most common adverse reactions are: palpitations, chest pain, tachycardia, headache, dizziness, tremor and nervousness. (6)

To report SUSPECTED ADVERSE REACTIONS, contact Akorn, Inc. at 1-800-932-5676 or FDA at 1-800-FDA-1088 or www.fda.gov/medwatch.

7 DRUG INTERACTIONS

- Other short-acting sympathomimetic aerosol bronchodilators and adrenergic drugs: May potentiate effect. (7.1)
- Beta-blockers: May block bronchodilatory effects of beta-agonists and produce severe bronchospasm. Patients with asthma should not normally be treated with beta-blockers. (7.2)
- Diuretic: May worsen electrocardiographic changes or hypokalemia associated with diuretic may worsen. Consider monitoring potassium levels. (7.3)
- Digoxin: May decrease serum digoxin levels. Consider monitoring digoxin levels. (7.4)
- Monoamine oxidase inhibitors (MAOs) or tricyclic antidepressants: May potentiate effect of albuterol on the cardiovascular system. (7.5)

FULL PRESCRIBING INFORMATION

1 INDICATIONS AND USAGE

XOPENEX (levalbuterol HCl) Inhalation Solution is indicated for the treatment or prevention of bronchospasm in adults, adolescents, and children 6 years of age and older with reversible obstructive airway disease.

2 DOSAGE AND ADMINISTRATION

XOPENEX Inhalation Solution is for oral inhalation only. Administer by nebulization using with a standard jet nebulizer (with a face mask or mouthpiece) connected to an air compressor. Do not exceed recommended dose.

Children 6 to 11 years old: The recommended dosage of XOPENEX Inhalation Solution for patients 6 to11 years old is 0.31 mg administered three times a day, by nebulization. Routine dosing should not exceed 0.63 mg three times a day.

Adults and Adolescents ≥12 years old: The recommended starting dosage of XOPENEX Inhalation Solution for patients 12 years of age and older is 0.63 mg administered three times a day, every 6 to 8 hours, by nebulization.

Patients 12 years of age and older with more severe asthma or patients who do not respond adequately to a dose of 0.63 mg of XOPENEX Inhalation Solution may benefit from a dosage of 1.25 mg three times a day.

Patients receiving the highest dose of XOPENEX Inhalation Solution should be monitored closely for adverse systemic effects, and the risks of such effects should be balanced against the potential for improved efficacy.

The use of XOPENEX Inhalation Solution can be continued as medically indicated to help control recurring bouts of bronchospasm. During this time, most patients gain optimal benefit from regular use of the inhalation solution.

If a previously effective dosage regimen fails to provide the usual response this may be a marker of destabilization of asthma and requires reevaluation of the patient and the treatment regimen, giving special consideration to the possible need for anti-inflammatory treatment, e.g., corticosteroids.

The drug compatibility (physical and chemical), efficacy, and safety of XOPENEX Inhalation Solution when mixed with other drugs in a nebulizer have not been established.

The safety and efficacy of XOPENEX Inhalation Solution have been established in clinical trials when administered using the PARI LC Jet™ and PARI LC Plus™ nebulizers, and the PARI Master® Dura-Neb® 2000 and Dura-Neb® 3000 compressors. The safety and efficacy of XOPENEX Inhalation Solution when administered using other nebulizer systems have not been established.

3 DOSAGE FORMS AND STRENGTHS

Inhalation Solution 3 mL unit-dose, vials in three dosage strengths of levalbuterol; 0.31 mg, 0.63 mg, 1.25 mg. Each strength of XOPENEX Inhalation Solution is available in a shelf carton containing one or more foil pouches, each containing 12 unit-dose vials.

4 CONTRAINDICATIONS

XOPENEX Inhalation Solution is contraindicated in patients with a history of hypersensitivity to levalbuterol or racemic albuterol. Reactions have included urticaria, angioedema, rash, bronchospasm, anaphylaxis, and oropharyngeal edema [see Warnings and Precautions (5.6)].

5 WARNINGS AND PRECAUTIONS

5.1 Paradoxical Bronchospasm

XOPENEX Inhalation Solution can produce paradoxical bronchospasm, which may be life-threatening. If paradoxical bronchospasm occurs, XOPENEX Inhalation Solution should be discontinued immediately and alternative therapy instituted. It should be recognized that paradoxical bronchospasm, when associated with inhaled formulations, frequently occurs with the first use of a new vial.

5.2 Deterioration of Asthma

Asthma may deteriorate acutely over a period of hours or chronically over several days or longer. If the patient needs more doses of XOPENEX Inhalation Solution than usual, this may be a marker of destabilization of asthma and requires reevaluation of the patient and treatment regimen, giving special consideration to the possible need for anti-inflammatory treatment, e.g., corticosteroids.

5.3 Use of Anti-Inflammatory Agents

XOPENEX Inhalation Solution is not a substitute for corticosteroids. The use of beta-adrenergic agonist alone may not be adequate to control asthma in many patients. Early consideration should be given to adding anti-inflammatory agents, e.g., corticosteroids, to the therapeutic regimen.

5.4 Cardiovascular Effects

XOPENEX Inhalation Solution, like other beta-adrenergic agonists, can produce clinically significant cardiovascular effects in some patients, as measured by heart rate, blood pressure, and symptoms. Although such effects are uncommon after administration of XOPENEX Inhalation Solution at recommended doses, if they occur, the drug may need to be discontinued. In addition, beta-agonists have been reported to produce electrocardiogram (ECG) changes, such as flattening of the t-wave, prolongation of the QTc interval, and ST segment depression. The clinical significance of these findings is unknown. Therefore, XOPENEX Inhalation Solution, like all sympathomimetic amines, should be used with caution in patients with cardiovascular disorders, especially coronary insufficiency, cardiac arrhythmias, and hypertension.

5.5 Do Not Exceed Recommended Dose

Do not exceed the recommended dose. Fatalities have been reported in association with excessive use of inhaled sympathomimetic drugs in patients with asthma. The exact cause of death is unknown, but cardiac arrest following an unexpected development of a severe acute asthmatic crisis and subsequent hypoxia is suspected.

5.6 Immediate Hypersensitivity Reactions

Immediate hypersensitivity reactions may occur after administration of levalbuterol or racemic albuterol. Reactions have included urticaria, angioedema, rash, bronchospasm, anaphylaxis, and oropharyngeal edema. The potential for hypersensitivity must be considered in the clinical evaluation of patients who experience immediate hypersensitivity reactions while receiving XOPENEX Inhalation Solution.

5.7 Coexisting Conditions

XOPENEX Inhalation Solution, like all sympathomimetic amines, should be used with caution in patients with cardiovascular disorders, especially coronary insufficiency, hypertension, and cardiac arrhythmias; in patients with convulsive disorders, hyperthyroidism, or diabetes mellitus; and in patients who are unusually responsive to sympathomimetic amines. Clinically significant changes in systolic and diastolic blood pressure have been seen in individual patients and could be expected to occur in some patients after the use of any beta-adrenergic bronchodilator.

Changes in blood glucose may occur. Large doses of intravenous racemic albuterol have been reported to aggravate preexisting diabetes mellitus and ketoacidosis.

5.8 Hypokalemia

As with other beta-adrenergic agonist medications, XOPENEX Inhalation Solution may produce significant hypokalemia in some patients, possibly through intracellular shunting, which has the potential to produce adverse cardiovascular effects. The decrease is usually transient, not requiring supplementation.

6 ADVERSE REACTIONS

The following serious adverse reactions are described below and elsewhere in the labeling:

- Paradoxical bronchospasm [see Warnings and Precautions (5.1)]
- Cardiovascular effects [see Warnings and Precautions (5.4)]
- Immediate hypersensitivity reactions [see Warnings and Precautions (5.6)]
- Hypokalemia [see Warnings and Precautions (5.8)]

6.1 Clinical Trials Experience

Because clinical trials are conducted under widely varying conditions, adverse reaction rates observed in the clinical trials of the drug cannot be directly compared with rates in the clinical trials of another drug and may not reflect the rates observed in practice.

Adults and Adolescents 12 Years of Age and Older

Adverse reaction information concerning XOPENEX Inhalation Solution in adults and adolescents is derived from one 4-week, multicenter, randomized, double-blind, active-, and placebo-controlled trial in 362 patients with asthma 12 years of age and older. Adverse reactions reported in ≥2% of patients receiving XOPENEX Inhalation Solution or racemic albuterol and more frequently than in patients receiving placebo are listed in Table 1.

Table 1: Adverse Reactions Reported in a 4-Week, Controlled Clinical Trial in Adults and Adolescents ≥12 Years Old
 | Percent of Patientsa
Body System Preferred Term | Placebo (n=75) | XOPENEX 1.25 mg (n=73) | XOPENEX 0.63 mg (n=72) |  | Racemic albuterol 2.5 mg (n=74)
Body as a Whole
Allergic reaction | 1.3 | 0 | 0 |  | 2.7
Flu syndrome | 0 | 1.4 | 4.2 |  | 2.7
Accidental injury | 0 | 2.7 | 0 |  | 0
Pain | 1.3 | 1.4 | 2.8 |  | 2.7
Back pain | 0 | 0 | 0 |  | 2.7
Cardiovascular System
Tachycardia | 0 | 2.7 | 2.8 |  | 2.7
Migraine | 0 | 2.7 | 0 |  | 0
Digestive System
Dyspepsia | 1.3 | 2.7 | 1.4 |  | 1.4
Musculoskeletal System
Leg cramps | 1.3 | 2.7 | 0 |  | 1.4
Central Nervous System
Dizziness | 1.3 | 2.7 | 1.4 |  | 0
Hypertonia | 0 | 0 | 0 |  | 2.7
Nervousness | 0 | 9.6 | 2.8 |  | 8.1
Tremor | 0 | 6.8 | 0 |  | 2.7
Anxiety | 0 | 2.7 | 0 |  | 0
Respiratory System
Cough increased | 2.7 | 4.1 | 1.4 |  | 2.7
Infection viral | 9.3 | 12.3 | 6.9 |  | 12.2
Rhinitis | 2.7 | 2.7 | 11.1 |  | 6.8
Sinusitis | 2.7 | 1.4 | 4.2 |  | 2.7
Turbinate edema | 0 | 1.4 | 2.8 |  | 0
a One treatment group, racemic albuterol 1.25 mg, with 68 subjects is omitted.

The incidence of certain systemic beta-adrenergic adverse reactions (e.g., tremor, nervousness) was slightly less in the XOPENEX Inhalation Solution 0.63 mg group compared with the other active treatment groups. The clinical significance of these small differences is unknown.

Changes in heart rate 15 minutes after drug administration and in plasma glucose and potassium 1 hour after drug administration on day 1 and day 29 were clinically comparable in the XOPENEX Inhalation Solution 1.25 mg and racemic albuterol 2.5 mg groups (see Table 2). Changes in heart rate and plasma glucose were slightly less in the XOPENEX Inhalation Solution 0.63 mg group compared with the other active treatment groups (see Table 2). The clinical significance of these small differences is unknown. After 4 weeks, effects on heart rate, plasma glucose, and plasma potassium were generally diminished compared with day 1 in all active treatment groups.

Table 2: Mean Changes from Baseline Heart Rate at 15 Minutes and Glucose and Potassium at 1 Hour after First Dose (Day 1) in Adults and Adolescents ≥12 Years Old
 | Mean Changes (day 1)
Treatment | Heart Rate (bpm) | Glucose (mg/dL) | Potassium (mEq/L)
XOPENEX 0.63 mg, n=72 | 2.4 | 4.6 | -0.2
XOPENEX 1.25 mg, n=73 | 6.9 | 10.3 | -0.3
Racemic albuterol 2.5 mg, n=74 | 5.7 | 8.2 | -0.3
Placebo, n=75 | -2.8 | -0.2 | -0.2

No other clinically relevant laboratory abnormalities related to administration of XOPENEX Inhalation Solution were observed in this study.

In the clinical trials, a slightly greater number of serious adverse events, discontinuations due to adverse events, and clinically significant ECG changes were reported in patients who received XOPENEX 1.25 mg compared with the other active treatment groups.

The following adverse reactions, considered potentially related to XOPENEX, occurred in less than 2% of the 292 subjects who received XOPENEX and more frequently than in patients who received placebo in any clinical trial:

Body as a Whole: | chills, pain, chest pain
Cardiovascular System: | ECG abnormal, ECG change, hypertension, hypotension, syncope
Digestive System: | diarrhea, dry mouth, dry throat, dyspepsia, gastroenteritis, nausea
Hemic and Lymphatic System: | lymphadenopathy
Musculoskeletal System: | leg cramps, myalgia
Nervous System: | anxiety, hyperesthesia of the hand, insomnia, paresthesia, tremor
Special Senses: | eye itch

The following reactions, considered potentially related to XOPENEX, occurred in less than 2% of the treated subjects but at a frequency less than in patients who received placebo: asthma exacerbation, cough increased, wheezing, sweating, and vomiting.

Pediatric Patients 6 to 11 Years of Age

Adverse reaction information concerning XOPENEX Inhalation Solution in pediatric patients is derived from one 3-week, multicenter, randomized, double-blind, active-, and placebo-controlled trial in 316 pediatric patients 6 to 11 years of age. Adverse reactions reported in ≥2% of patients in any treatment group and more frequently than in patients receiving placebo are listed in Table 3.

Table 3: Most Frequently Reported Adverse Reactions (≥2% in Any Treatment Group) and Those Reported More Frequently Than in Placebo during the Double-Blind Period (ITT Population, 6 to 11 Years Old)
 | Percent of Patients
Body System Preferred Term | Placebo (n=59) | XOPENEX 0.31 mg (n=66) | XOPENEX 0.63 mg (n=67) | Racemic albuterol 1.25 mg (n=64) | Racemic albuterol 2.5 mg (n=60)
Body as a Whole
Abdominal pain | 3.4 | 0 | 1.5 | 3.1 | 6.7
Accidental injury | 3.4 | 6.1 | 4.5 | 3.1 | 5.0
Asthenia | 0 | 3.0 | 3.0 | 1.6 | 1.7
Fever | 5.1 | 9.1 | 3.0 | 1.6 | 6.7
Headache | 8.5 | 7.6 | 11.9 | 9.4 | 3.3
Pain | 3.4 | 3.0 | 1.5 | 4.7 | 6.7
Viral infection | 5.1 | 7.6 | 9.0 | 4.7 | 8.3
Digestive System
Diarrhea | 0 | 1.5 | 6.0 | 1.6 | 0
Hemic and Lymphatic
Lymphadenopathy | 0 | 3.0 | 0 | 1.6 | 0
Musculoskeletal System
Myalgia | 0 | 0 | 1.5 | 1.6 | 3.3
Respiratory System
Asthma | 5.1 | 9.1 | 9.0 | 6.3 | 10.0
Pharyngitis | 6.8 | 3.0 | 10.4 | 0 | 6.7
Rhinitis | 1.7 | 6.1 | 10.4 | 3.1 | 5.0
Skin and Appendages
Eczema | 0 | 0 | 0 | 0 | 3.3
Rash | 0 | 0 | 7.5 | 1.6 | 0
Urticaria | 0 | 0 | 3.0 | 0 | 0
Special Senses
Otitis media | 1.7 | 0 | 0 | 0 | 3.3
Note: Subjects may have more than one adverse event per body system and preferred term.

Changes in heart rate, plasma glucose, and serum potassium are shown in Table 4. The clinical significance of these small differences is unknown.

Table 4: Mean Changes from Baseline Heart Rate at 30 Minutes and Glucose and Potassium at 1 Hour after First Dose (Day 1) and Last Dose (Day 21) in Children 6 to 11 Years Old
 | Mean Changes (Day 1)
Treatment | Heart Rate (bpm) | Glucose (mg/dL) | Potassium (mEq/L)
XOPENEX 0.31 mg, n=66 | 0.8 | 4.9 | -0.31
XOPENEX 0.63 mg, n=67 | 6.7 | 5.2 | -0.36
Racemic albuterol 1.25 mg, n=64 | 6.4 | 8.0 | -0.27
Racemic albuterol 2.5 mg, n=60 | 10.9 | 10.8 | -0.56
Placebo, n=59 | -1.8 | 0.6 | -0.05
 | Mean Changes (Day 21)
Treatment | Heart Rate (bpm) | Glucose (mg/dL) | Potassium (mEq/L)
XOPENEX 0.31 mg, n=60 | 0 | 2.6 | -0.32
XOPENEX 0.63 mg, n=66 | 3.8 | 5.8 | -0.34
Racemic albuterol 1.25 mg, n=62 | 5.8 | 1.7 | -0.18
Racemic albuterol 2.5 mg, n=54 | 5.7 | 11.8 | -0.26
Placebo, n=55 | -1.7 | 1.1 | -0.04

6.2 Post-marketing Experience

In addition to the adverse reactions reported in clinical trials, the following adverse reactions have been observed in postapproval use of XOPENEX Inhalation Solution. Because these reactions are reported voluntarily from a population of uncertain size, it is not always possible to reliably estimate their frequency or establish a causal relationship to drug exposure. These events have been chosen for inclusion due to their seriousness, their frequency of reporting, or their likely beta-mediated mechanism: angioedema, anaphylaxis, arrhythmias (including atrial fibrillation, supraventricular tachycardia, extrasystoles), asthma, chest pain, cough increased, dysphonia, dyspnea, gastroesophageal reflux disease (GERD), metabolic acidosis, nausea, nervousness, rash, tachycardia, tremor, urticaria.

In addition, XOPENEX Inhalation Solution, like other sympathomimetic agents, can cause adverse reactions such as hypertension, angina, vertigo, central nervous system stimulation, sleeplessness, headache, and drying or irritation of the oropharynx.

7 DRUG INTERACTIONS

7.1 Short-Acting Bronchodilators

Avoid concomitant use of other short-acting sympathomimetic bronchodilators or epinephrine in patients being treated with XOPENEX Inhalation Solution. If additional adrenergic drugs are to be administered by any route, they should be used with caution to avoid deleterious cardiovascular effects.

7.2 Beta-blockers

Beta-adrenergic receptor blocking agents not only block the pulmonary effect of beta-adrenergic agonists such as XOPENEX Inhalation Solution, but may produce severe bronchospasm in asthmatic patients. Therefore, patients with asthma should not normally be treated with beta-blockers. However, under certain circumstances, e.g., prophylaxis after myocardial infarction, there may be no acceptable alternatives to the use of beta-adrenergic blocking agents in patients with asthma. In this setting, cardioselective beta-blockers should be considered, although they should be administered with caution.

7.3 Diuretics

The ECG changes or hypokalemia that may result from the administration of non-potassium-sparing diuretics (such as loop and thiazide diuretics) can be acutely worsened by beta-agonists, especially when the recommended dose of the beta-agonist is exceeded. Although the clinical significance of these effects is not known, caution is advised in the coadministration of beta-agonists with non-potassium-sparing diuretics. Consider monitoring potassium levels.

7.4 Digoxin

Mean decreases of 16% and 22% in serum digoxin levels were demonstrated after single-dose intravenous and oral administration of racemic albuterol, respectively, to normal volunteers who had received digoxin for 10 days. The clinical significance of these findings for patients with obstructive airway disease who are receiving XOPENEX Inhalation Solution and digoxin on a chronic basis is unclear. Nevertheless, it would be prudent to carefully evaluate the serum digoxin levels in patients who are currently receiving digoxin and XOPENEX Inhalation Solution.

7.5 Monoamine Oxidase Inhibitors or Tricyclic Antidepressants

XOPENEX Inhalation Solution should be administered with extreme caution to patients being treated with monoamine oxidase inhibitors or tricyclic antidepressants, or within 2 weeks of discontinuation of such agents, because the action of levalbuterol on the vascular system may be potentiated. Consider alternative therapy in patients taking MAO inhibitors or tricyclic antidepressants.

8 USE IN SPECIFIC POPULATIONS

8.1 Pregnancy

Pregnancy Exposure Registry

There is a pregnancy exposure registry that monitors pregnancy outcomes in women exposed to asthma medication, including XOPENEX, during pregnancy. To enroll in MotherToBaby Pregnancy Studies' Asthma & Pregnancy Study or for more information about the registry, call 1-877-311-8972 or visit www.mothertobaby.org/ongoing-study/asthma.

Risk Summary

There are no adequate and well-controlled studies of XOPENEX Inhalation Solution in pregnant women. There are clinical considerations with the use of XOPENEX Inhalation Solution in pregnant women [see Clinical Considerations].

Following oral administration of levelbuterol HCl to pregnant rabbits, there was no evidence of teratogenicity at doses up to 25 mg/kg/day [approximately 108 times the maximum recommended human daily inhalation dose (MRHDID) of levalbuterol HCl for adults on a mg/m^2 basis]; however, racemic albuterol sulfate was teratogenic in mice (cleft palate) and rabbits (cramioschisis) at doses slightly higher than the human therapeutic range (see Data).

The estimated background risk of major birth defects and miscarriage for the indicated populations(s) are unknown. In the U.S. general population, the estimated risk of major birth defects and miscarriage in clinically recognized pregnancies is 2 to 4% and 15 to 20% respectively.

Clinical Considerations

Disease-Associated Maternal and/or Embryo/Fetal Risk

In women with poorly or moderately controlled asthma, there is an increased risk of preeclampsia in the mother and prematurity, low birth weight, and small for gestational age in the neonate. Pregnant women should be closely monitored and medication adjusted as necessary to maintain optimal control.

Labor or Delivery

Because of the potential for beta-adrenergic agonists to interfere with uterine contractility, the use of XOPENEX Inhalation Solution for the treatment of bronchospasm during labor should be restricted to those patients for whom the benefits clearly outweigh the risk.

XOPENEX Inhalation Solution has not been approved for the management of preterm labor. The benefit-risk ratio when XOPENEX is administered for tocolysis has not been established. Serious adverse reactions, including maternal pulmonary edema, have been reported during or following treatment of premature labor with beta2-agonists, including racemic albuterol.

Data

Animal Data

The oral administration of levalbuterol HCl to pregnant New Zealand White rabbits during the period of organogenesis found no evidence of teratogenicity at doses up to 25 mg/kg/day (approximately 108 times the MRHDID of levalbuterol HCl for adults on a mg/m^2 basis). In a rat developmental study, racemic albuterol sulfate administered by inhalation did not produce any teratogenic effects at exposures approximately 63 times the MRHDID (on a mg/m^2 basis at a maternal dose of 10.5 mg/kg).

However, other developmental studies with the racemic albuterol sulfate, did result in teratogenic effects in mice and rabbits at doses slightly higher than the human therapeutic range. In a rabbit developmental study, orally administered albuterol sulfate induced cranioschisis in 7 of 19 fetuses (37%) at approximately 215 times the MRHDID for adults (on a mg/m^2 basis at a maternal dose of 50 mg/kg). In a mouse developmental study, subcutaneously administered albuterol sulfate produced cleft palate formation in 5 of 111 (4.5%) fetuses at an exposure approximately 0.3 times the MRHDID for adults (on a mg/m^2 basis at a maternal dose of 0.25 mg/kg/day) and in 10 of 108 (9.3%) fetuses at approximately 3 times the MRHDID (on a mg/m^2 basis at a maternal dose of 2.5 mg/kg/day). Similar effects were not observed at approximately 0.03 times the MRHDID for adults on a mg/m^2 basis at a maternal dose of 0.025 mg/kg/day (i.e., less than the therapeutic dose). Cleft palate also occurred in 22 of 72 (30.5%) fetuses from females treated subcutaneously with isoproterenol (positive control).

8.2 Lactation

Risk Summary

There are no available data on the presence of levalbuterol in human milk, the effects on the breastfed child, or the effects on milk production.

The developmental and health benefits of breastfeeding should be considered along with the mother's clinical need for XOPENEX Inhalation Solution and any potential adverse effects on the breastfed child from XOPENEX Inhalation Solution or from the underlying maternal condition.

8.4 Pediatric Use

Pediatric Patients 6 Years of Age and Older

The safety and efficacy of XOPENEX Inhalation Solution have been established in pediatric patients 6 years of age and older in an adequate and well-controlled clinical trial [see Adverse Reactions (6) and Clinical Studies (14)].

Pediatric Patients less than 6 Years of Age

XOPENEX Inhalation Solution is not indicated for pediatric patients less than 6 years of age.

Clinical trials with XOPENEX Inhalation Solution in this age group failed to meet the primary efficacy endpoint and demonstrated an increased number of asthma-related adverse reactions following chronic XOPENEX treatment.

XOPENEX Inhalation Solution was studied in 379 pediatric patients less than 6 years of age with asthma or reactive airway disease - (291 patients 2 to 5 years of age, and 88 patients from birth to less than 2 years of age). Efficacy and safety data for XOPENEX Inhalation Solution in this age group are primarily available from one 3-week, multicenter, randomized, double-blind, active and placebo-controlled study (Study 1) in 211 pediatric patients between the ages of 2 and 5 years, of whom 119 received XOPENEX Inhalation Solution. Over the 3 week treatment period, there were no significant treatment differences in the Pediatric Asthma Questionnaire (PAQ) total score between groups receiving XOPENEX Inhalation Solution 0.31 mg, XOPENEX Inhalation Solution 0.63 mg, racemic albuterol, and placebo. Additional safety data following chronic dosing is available from a 4-week, multicenter, randomized, modified-blind, placebo-controlled study (Study 2) of 196 patients between the ages of birth and 3 years, of whom 63 received open-label XOPENEX Inhalation Solution. In these two studies, treatment-emergent asthma exacerbations or asthma-related adverse reactions and treatment discontinuations due to asthma occurred at a higher frequency in XOPENEX Inhalation-treated subjects compared to control (Table 5). Other adverse reactions were consistent with those observed in the clinical trial population of patients 6 years of age and older [see Adverse Reactions (6.1)].

Table 5: Asthma-related Adverse Reactions in 3- and 4-Week Clinical Trials in Children Birth to <6 Years of Age
 | Asthma Exacerbations* n (%) | Treatment Discontinuations due to Asthma n (%) | Asthma-related Adverse Reactions** n (%)
Study 1
XOPENEX 0.31 mg, n=58 | 6 (10) | 4 (7) | —
XOPENEX 0.63 mg, n=51 | 7 (14) | 6 (12) | —
Racemic albuterol, n=52 | 3 (6) | 2 (4) | —
Placebo, n=50 | 2 (4) | 2 (4) | —
Study 2
XOPENEX 0.31 mg, n=63 | — | 2 (3) | 6 (10)
Levalbuterol HFA inhalation aerosol, n=65 | — | 1 (2) | 8 (12)
Placebo, n=68 | — | 0 | 3 (4)
* Asthma exacerbation defined as worsening of asthma symptoms or pulmonary function that required any of the following: emergency department visit, hospitalization, therapeutic intervention with oral or parenteral steroids, unscheduled clinic visit to treat acute asthma symptoms.
** Includes the following Preferred Terms (whether considered by the investigator to be related or unrelated to drug): asthma, cough, hypoxia, status asthmaticus, tachypnea.

8.5 Geriatric Use

Clinical studies of XOPENEX Inhalation Solution did not include sufficient numbers of subjects aged 65 years and older to determine whether they respond differently from younger subjects. Only 5 patients 65 years of age and older were treated with XOPENEX Inhalation Solution in a 4-week clinical study [see Clinical Pharmacology (12) and Clinical Studies (14)] (n=2 for 0.63 mg and n=3 for 1.25 mg). In these patients, bronchodilation was observed after the first dose on day 1 and after 4 weeks of treatment. In general, patients 65 years of age and older should be started at a dose of 0.63 mg of XOPENEX Inhalation Solution. If clinically warranted due to insufficient bronchodilator response, the dose of XOPENEX Inhalation Solution may be increased in elderly patients as tolerated, in conjunction with frequent clinical and laboratory monitoring, to the maximum recommended daily dose [see Dosage and Administration (2)].

8.6 Renal Impairment

Albuterol is known to be substantially excreted by the kidney, and the risk of toxic reactions may be greater in patients with impaired renal function. Because elderly patients are more likely to have decreased renal function, care should be taken in dose selection, and it may be useful to monitor renal function.

10 OVERDOSAGE

The expected symptoms with overdosage are those of excessive beta-adrenergic receptor stimulation and/or occurrence or exaggeration of any of the symptoms listed under Adverse Reactions (6), e.g., seizures, angina, hypertension or hypotension, tachycardia with rates up to 200 beats/min., arrhythmias, nervousness, headache, tremor, dry mouth, palpitation, nausea, dizziness, fatigue, malaise, and sleeplessness. Hypokalemia also may occur. As with all sympathomimetic medications, cardiac arrest and even death may be associated with the abuse of XOPENEX Inhalation Solution. Treatment consists of discontinuation of XOPENEX Inhalation Solution together with appropriate symptomatic therapy. The judicious use of a cardioselective beta-receptor blocker may be considered, bearing in mind that such medication can produce bronchospasm. There is insufficient evidence to determine if dialysis is beneficial for overdosage of XOPENEX Inhalation Solution.

11 DESCRIPTION

XOPENEX Inhalation Solution is a sterile, clear, colorless, preservative-free solution of the hydrochloride salt of levalbuterol, the (R)-enantiomer of the drug substance racemic albuterol. Levalbuterol HCl is a relatively selective beta2-adrenergic receptor agonist [see Clinical Pharmacology (12)]. The chemical name for levalbuterol HCl is (R)-α^1-[[(1,1-dimethylethyl) amino]methyl]-4-hydroxy-1,3-benzenedimethanol hydrochloride, and its established chemical structure is as follows:

The molecular weight of levalbuterol HCl is 275.8, and its empirical formula is C13H21NO3•HCl. It is a white to off-white, crystalline solid, with a melting point of approximately 187°C and solubility of approximately 180 mg/mL in water.

Levalbuterol HCl is the USAN modified name for (R)-albuterol HCl in the United States.

XOPENEX Inhalation Solution is supplied in unit-dose vials and requires no dilution before administration by nebulization. Each 3 mL unit-dose vial contains 0.31 mg of levalbuterol (as 0.36 mg of levalbuterol HCl) or 0.63 mg of levalbuterol (as 0.73 mg of levalbuterol HCl) or 1.25 mg of levalbuterol (as 1.44 mg of levalbuterol HCl), sodium chloride to adjust tonicity, and sulfuric acid to adjust the pH to 4.0 (3.3 to 4.5).

12 CLINICAL PHARMACOLOGY

12.1 Mechanism of Action

Activation of beta2-adrenergic receptors on airway smooth muscle leads to the activation of adenylate cyclase and to an increase in the intracellular concentration of cyclic-3′, 5′-adenosine monophosphate (cyclic AMP). The increase in cyclic AMP is associated with the activation of protein kinase A, which in turn inhibits the phosphorylation of myosin and lowers intracellular ionic calcium concentrations, resulting in muscle relaxation. Levalbuterol relaxes the smooth muscles of all airways, from the trachea to the terminal bronchioles. Increased cyclic AMP concentrations are also associated with the inhibition of release of mediators from mast cells in the airway. Levalbuterol acts as a functional antagonist to relax the airway irrespective of the spasmogen involved, thus protecting against all bronchoconstrictor challenges. While it is recognized that beta2-adrenergic receptors are the predominant receptors on bronchial smooth muscle, data indicate that there are beta-receptors in the human heart, 10% to 50% of which are beta2-adrenergic receptors. The precise function of these receptors has not been established [see Warnings and Precautions (5.4)]. However, all beta-adrenergic agonist drugs can produce a significant cardiovascular effect in some patients, as measured by pulse rate, blood pressure, symptoms, and/or electrocardiographic changes.

12.2 Pharmacodynamics

Adults and Adolescents ≥12 Years Old

In a randomized, double-blind, placebo-controlled, cross-over study, 20 adults with mild-to-moderate asthma received single doses of XOPENEX Inhalation Solution (0.31 mg, 0.63 mg, and 1.25 mg) and racemic albuterol sulfate inhalation solution (2.5 mg). All doses of active treatment produced a significantly greater degree of bronchodilation (as measured by percent change from pre-dose mean FEV1) than placebo, and there were no significant differences between any of the active treatment arms. The bronchodilator responses to 1.25 mg of XOPENEX Inhalation Solution and 2.5 mg of racemic albuterol sulfate inhalation solution were clinically comparable over the 6-hour evaluation period, except for a slightly longer duration of action (>15% increase in FEV1 from baseline) after administration of 1.25 mg of XOPENEX Inhalation Solution. Systemic beta-adrenergic adverse effects were observed with all active doses and were generally dose-related for (R)-albuterol. XOPENEX Inhalation Solution at a dose of 1.25 mg produced a slightly higher rate of systemic beta-adrenergic adverse effects than the 2.5 mg dose of racemic albuterol sulfate inhalation solution.

In a randomized, double-blind, placebo-controlled, cross-over study, 12 adults with mild-to-moderate asthma were challenged with inhaled methacholine chloride 20 and 180 minutes following administration of a single dose of 2.5 mg of racemic albuterol sulfate, 1.25 mg of XOPENEX, 1.25 mg of (S)-albuterol, or placebo using a Pari LC Jet™ nebulizer. Racemic albuterol sulfate, XOPENEX, and (S)-albuterol had a protective effect against methacholine-induced bronchoconstriction 20 minutes after administration, although the effect of (S)-albuterol was minimal. At 180 minutes after administration, the bronchoprotective effect of 1.25 mg of XOPENEX was comparable to that of 2.5 mg of racemic albuterol sulfate. At 180 minutes after administration, 1.25 mg of (S)-albuterol had no bronchoprotective effect.

In a clinical study in adults with mild-to-moderate asthma, comparable efficacy (as measured by change from baseline FEV1) and safety (as measured by heart rate, blood pressure, ECG, serum potassium, and tremor) were demonstrated after a cumulative dose of 5 mg of XOPENEX Inhalation Solution (four consecutive doses of 1.25 mg administered every 30 minutes) and 10 mg of racemic albuterol sulfate inhalation solution (four consecutive doses of 2.5 mg administered every 30 minutes).

12.3 Pharmacokinetics

Adults and Adolescents ≥12 Years Old

The inhalation pharmacokinetics of XOPENEX Inhalation Solution were investigated in a randomized cross-over study in 30 healthy adults following administration of a single dose of 1.25 mg and a cumulative dose of 5 mg of XOPENEX Inhalation Solution and a single dose of 2.5 mg and a cumulative dose of 10 mg of racemic albuterol sulfate inhalation solution by nebulization using a PARI LC Jet™ nebulizer with a Dura-Neb® 2000 compressor.

Following administration of a single 1.25 mg dose of XOPENEX Inhalation Solution, exposure to (R)-albuterol (AUC of 3.3 ng•hr/mL) was approximately 2-fold higher than following administration of a single 2.5 mg dose of racemic albuterol inhalation solution (AUC of 1.7 ng•hr/mL) (see Table 5). Following administration of a cumulative 5 mg dose of XOPENEX Inhalation Solution (1.25 mg given every 30 minutes for a total of four doses) or a cumulative 10 mg dose of racemic albuterol inhalation solution (2.5 mg given every 30 minutes for a total of four doses), Cmax and AUC of (R)-albuterol were comparable (see Table 6).

Table 6: Mean (SD) Values for Pharmacokinetic Parameters in Healthy Adults
 | Single Dose |  |  | Cumulative Dose
 | XOPENEX 1.25 mg | Racemic albuterol sulfate 2.5 mg |  | XOPENEX 5 mg | Racemic albuterol sulfate 10 mg
Cmax (ng/mL) (R)-albuterol | 1.1 (0.45) | 0.8 (0.41)** |  | 4.5 (2.20) | 4.2 (1.51)**
Tmax (h)γ (R)-albuterol | 0.2 (0.17, 0.37) | 0.2 (0.17, 1.50) |  | 0.2 (–0.18*, 1.25) | 0.2 (–0.28*, 1.00)
AUC (ng•hr/mL) (R)-albuterol | 3.3 (1.58) | 1.7 (0.99)** |  | 17.4 (8.56) | 16.0 (7.12)**
T½ (h) (R)-albuterol | 3.3 (2.48) | 1.5 (0.61) |  | 4.0 (1.05) | 4.1 (0.97)
γ Median (Min, Max) reported for Tmax.
* A negative Tmax indicates Cmax occurred between first and last nebulizations.
** Values reflect only (R)-albuterol and do not include (S)-albuterol.

Children 6 to 11 Years Old

The pharmacokinetic parameters of (R)- and (S)-albuterol in children with asthma were obtained using population pharmacokinetic analysis. These data are presented in Table 7. For comparison, adult data obtained by conventional pharmacokinetic analysis from a different study also are presented in Table 7.

In children, AUC and Cmax of (R)-albuterol following administration of 0.63 mg XOPENEX Inhalation Solution were comparable to those following administration of 1.25 mg racemic albuterol sulfate inhalation solution.

When the same dose of 0.63 mg of XOPENEX Inhalation Solution was given to children and adults, the predicted Cmax of (R)-albuterol in children was similar to that in adults (0.52 vs. 0.56 ng/mL), while predicted AUC in children (2.55 ng•hr/mL) was about 1.5-fold higher than that in adults (1.65 ng•hr/mL). These data support lower doses for children 6 to 11 years old compared with the adult doses [see Dosage and Administration (2)].

Table 7: (R)-Albuterol Exposure in Adults and Pediatric Subjects (6 to 11 years)
 | Children 6 to 11 years |  |  |  |  | Adults ≥12 years
Treatment | XOPENEX 0.31 mg | XOPENEX 0.63 mg | Racemic albuterol 1.25 mg | Racemic albuterol 2.5 mg |  | XOPENEX 0.63 mg | XOPENEX 1.25 mg
AUC0-∞ (ng•hr/mL) c | 1.36 | 2.55 | 2.65 | 5.02 |  | 1.65 a | 3.3 b
Cmax (ng/mL) d | 0.303 | 0.521 | 0.553 | 1.08 |  | 0.56 a | 1.1 b
a The values are predicted by assuming linear pharmacokinetics
b The data obtained from Table 6
c Area under the plasma concentration curve from time 0 to infinity
d Maximum plasma concentration

Metabolism and Elimination

Information available in the published literature suggests that the primary enzyme responsible for the metabolism of albuterol enantiomers in humans is SULT1A3 (sulfotransferase). When racemic albuterol was administered either intravenously or via inhalation after oral charcoal administration, there was a 3- to 4-fold difference in the area under the concentration-time curves between the (R)- and (S)-albuterol enantiomers, with (S)-albuterol concentrations being consistently higher. However, without charcoal pretreatment, after either oral or inhalation administration the differences were 8- to 24-fold, suggesting that (R)-albuterol is preferentially metabolized in the gastrointestinal tract, presumably by SULT1A3.

The primary route of elimination of albuterol enantiomers is through renal excretion (80% to 100%) of either the parent compound or the primary metabolite. Less than 20% of the drug is detected in the feces. Following intravenous administration of racemic albuterol, between 25% and 46% of the (R)-albuterol fraction of the dose was excreted as unchanged (R)-albuterol in the urine.

Special Populations

Hepatic Impairment

The effect of hepatic impairment on the pharmacokinetics of XOPENEX Inhalation Solution has not been evaluated.

Renal Impairment

The effect of renal impairment on the pharmacokinetics of racemic albuterol was evaluated in 5 subjects with creatinine clearance of 7 to 53 mL/min, and the results were compared with those from healthy volunteers. Renal disease had no effect on the half-life, but there was a 67% decline in racemic albuterol clearance. Caution should be used when administering high doses of XOPENEX Inhalation Solution to patients with renal impairment [see Use in Specific Populations (8.6)].

13 NONCLINICAL TOXICOLOGY

13.1 Carcinogenesis, Mutagenesis, Impairment of Fertility

Although there have been no carcinogenesis studies with levalbuterol HCl, racemic albuterol sulfate has been evaluated for its carcinogenic potential.

In a 2-year study in Sprague-Dawley rats, dietary administration of racemic albuterol sulfate resulted in a significant dose-related increase in the incidence of benign leiomyomas of the mesovarium at doses of 2 mg/kg/day and greater (approximately 4 times the MRHDID of levalbuterol HCl for adults and approximately 5 times the MRHDID of levalbuterol HCl for children on a mg/m^2 basis). In an 18-month study in CD-1 mice and a 22-month study in the golden hamster, dietary administration of racemic albuterol sulfate showed no evidence of tumorigenicity. Dietary doses in CD-1 mice were up to 500 mg/kg/day (approximately 540 times the MRHDID of levalbuterol HCl for adults and approximately 630 times the MRHDID of levalbuterol HCl for children on a mg/m^2 basis) and doses in the golden hamster study were up to 50 mg/kg/day (approximately 90 times the MRHDID of levalbuterol HCl for adults on a mg/m^2 basis and approximately 105 times the MRHDID of levalbuterol HCl for children on a mg/m^2 basis).

Levalbuterol HCl was not mutagenic in the Ames test or the CHO/HPRT Mammalian Forward Gene Mutation Assay. Levalbuterol HCl was not clastogenic in the in vivo micronucleus test in mouse bone marrow. Racemic albuterol sulfate was not clastogenic in an in vitro chromosomal aberration assay in CHO cell cultures.

No fertility studies have been conducted with levalbuterol hydrochloride. Reproduction studies in rats using racemic albuterol sulfate demonstrated no evidence of impaired fertility at oral doses up to 50 mg/kg/day (approximately 108 times the maximum recommended daily inhalation dose of levalbuterol HCl for adults on a mg/m^2 basis).

14 CLINICAL STUDIES

Adults and Adolescents ≥12 Years Old

The safety and efficacy of XOPENEX Inhalation Solution were evaluated in a 4-week, multicenter, randomized, double-blind, placebo-controlled, parallel-group study in 362 adult and adolescent patients 12 years of age and older, with mild-to-moderate asthma (mean baseline FEV1 60% of predicted). Approximately half of the patients were also receiving inhaled corticosteroids. Patients were randomized to receive XOPENEX 0.63 mg, XOPENEX 1.25 mg, racemic albuterol sulfate 1.25 mg, racemic albuterol sulfate 2.5 mg, or placebo three times a day administered via a PARI LC Plus™ nebulizer and a Dura-Neb® portable compressor. Racemic albuterol delivered by a chlorofluorocarbon (CFC) metered-dose inhaler (MDI) was used on an as-needed basis as the rescue medication.

Efficacy, as measured by the mean percent change from baseline FEV1, was demonstrated for all active treatment regimens compared with placebo on day 1 and day 29. On both day 1 (see Figure 1) and day 29 (see Figure 2), 1.25 mg of XOPENEX demonstrated the largest mean percent change from baseline FEV1 compared with the other active treatments. A dose of 0.63 mg of XOPENEX and 2.5 mg of racemic albuterol sulfate produced a clinically comparable mean percent change from baseline FEV1 on both day 1 and day 29.

Figure 1: Mean Percent Change from Baseline FEV 1 on Day 1, Adults and Adolescents ≥12 years old

Figure 2: Mean Percent Change from Baseline FEV 1 on Day 29, Adults and Adolescents ≥12 years old

The mean time to onset of a 15% increase in FEV1 over baseline for levalbuterol at doses of 0.63 mg and 1.25 mg was approximately 17 minutes and 10 minutes, respectively, and the mean time to peak effect for both doses was approximately 1.5 hours after 4 weeks of treatment. The mean duration of effect, as measured by a >15% increase from baseline FEV1, was approximately 5 hours after administration of 0.63 mg of levalbuterol and approximately 6 hours after administration of 1.25 mg of levalbuterol after 4 weeks of treatment. In some patients, the duration of effect was as long as 8 hours.

Children 6 to 11 Years Old

A multicenter, randomized, double-blind, placebo- and active-controlled study was conducted in children with mild-to-moderate asthma (mean baseline FEV1 73% of predicted) (n=316). Following a 1-week placebo run-in, subjects were randomized to XOPENEX (0.31 or 0.63 mg), racemic albuterol (1.25 or 2.5 mg), or placebo, which were delivered three times a day for 3 weeks using a PARI LC Plus™ nebulizer and a Dura-Neb® 3000 compressor.

Efficacy, as measured by mean peak percent change from baseline FEV1, was demonstrated for all active treatment regimens compared with placebo on day 1 and day 21. Time profile FEV1 curves for day 1 and day 21 are shown in Figure 3 and Figure 4, respectively. The onset of effect (time to a 15% increase in FEV1 over test-day baseline) and duration of effect (maintenance of a >15% increase in FEV1 over test-day baseline) of levalbuterol were clinically comparable to those of racemic albuterol.

Figure 3: Mean Percent Change from Baseline FEV 1 on Day 1, Children 6 to 11 Years of Age

Figure 4: Mean Percent Change from Baseline FEV 1 on Day 21, Children 6 to 11 Years of Age

16 HOW SUPPLIED/STORAGE AND HANDLING

XOPENEX Inhalation Solution is supplied in 3 mL unit-dose, low-density polyethylene (LDPE) vials as a clear, colorless, sterile, preservative-free, aqueous solution, in three different strengths of levalbuterol (0.31 mg, 0.63 mg, 1.25 mg). Each strength of XOPENEX Inhalation Solution is available in a shelf-carton containing one or more foil pouches, each containing 12 unit-dose LDPE vials.

XOPENEX (levalbuterol HCl) Inhalation Solution, 0.31 mg (foil pouch label color green) contains 0.31 mg of levalbuterol (as 0.36 mg of levalbuterol HCl) and is available in cartons of 24 unit-dose LDPE vials (NDC 17478-172-24).

XOPENEX (levalbuterol HCl) Inhalation Solution, 0.63 mg (foil pouch label color yellow) contains 0.63 mg of levalbuterol (as 0.73 mg of levalbuterol HCl) and is available in cartons of 24 unit-dose LDPE vials (NDC 17478-173-24).

XOPENEX (levalbuterol HCl) Inhalation Solution, 1.25 mg (foil pouch label color red) contains 1.25 mg of levalbuterol (as 1.44 mg of levalbuterol HCl) and is available in cartons of 24 unit-dose LDPE vials (NDC 17478-174-24).

XOPENEX Inhalation Solution is also available as a concentrate in individually pouched 0.5 mL unit-dose vials containing 1.25 mg of levalbuterol (NDC 17478-171-30).

Storage: Store XOPENEX Inhalation Solution in the protective foil pouch at 20° to 25°C (68° to 77°F) [see USP Controlled Room Temperature]. Protect from light and excessive heat. Keep unopened vials in the foil pouch. Once the foil pouch is opened, the vials should be used within 2 weeks. Vials removed from the pouch, if not used immediately, should be protected from light and used within 1 week. Discard any vial if the solution is not colorless.

17 PATIENT COUNSELING INFORMATION

See FDA-approved patient labeling (Patient Information and Instructions for Using XOPENEX Inhalation Solution).

Patients should be given the following information:

Hypersensitivity

Query patients about previously experienced hypersensitivity to levalbuterol or racemic albuterol and counsel patients to report any hypersensitivity reactions to their physician.

Frequency of Use

Inform patients not to increase the dose or use XOPENEX Inhalation Solution more frequently than recommended without consulting their physician. If patients find that treatment with XOPENEX Inhalation Solution becomes less effective for symptomatic relief, symptoms become worse, or they need to use the product more frequently than usual, they should seek medical attention immediately.

Paradoxical Bronchospasm

Inform patients that XOPENEX Inhalation Solution can produce paradoxical bronchospasm. Instruct patients to discontinue XOPENEX Inhalation Solution if paradoxical bronchospasm occurs.

Concomitant Drug Use

Inform patients using XOPENEX Inhalation Solution, that other inhaled drugs and asthma medications should be taken only as directed by their physician.

Common Adverse Reactions

Advise patients of the common adverse reactions of treatment with XOPENEX Inhalation Solution including palpitations, chest pain, fast heart rate, headache, dizziness, tremor and nervousness.

Pregnancy

Advise patients who are pregnant or nursing to contact their physician about the use of XOPENEX Inhalation Solution.

There is a pregnancy exposure registry that monitors pregnancy outcomes in women exposed to asthma medication, including XOPENEX, during pregnancy. To enroll in the Asthma & Pregnancy Study or for more information about the registry, call 1-877-311-8972 or visit www.mothertobaby.org/ongoing-study/asthma [see Use in Specific Populations (8.1)].

General Information on Storage and Use

Advise patients to store XOPENEX Inhalation Solution in the foil pouch between 20° to 25°C (68° to 77°F), protected from light and excessive heat. Do not use after the expiration date stamped on the container. Store unused vials in the protective foil pouch. Once the foil pouch is opened, use the vials within 2 weeks. Use vials removed from the pouch immediately, or protect from light and use within 1 week. Discard any vial if the solution is not colorless.

Advise patients not to mix XOPENEX Inhalation Solution with other drugs in a nebulizer.

AKORN
Distributed by: Akorn, Inc.
Lake Forest, IL 60045

Manufactured for: Oak Pharmaceuticals, Inc.

For customer service, call 1-800-932-5676.
To report adverse events, call 1-800-932-5676.

For medical information, call 1-800-932-5676.

Xopenex is a registered trademark of Sunovion Pharmaceuticals Inc. and is used under license.

XP00N December 2018
AKNX024-642R01

PATIENT INFORMATION

XOPENEX® (pronounced zō-pen-eks)

(levalbuterol hydrochloride)

Inhalation Solution

0.31 mg, 0.63 mg, 1.25 mg

3 mL Unit-Dose Vials

For Oral Inhalation Only

XOPENEX Inhalation Solution is only for use with a nebulizer.

Read this Patient Information before you start to use XOPENEX Inhalation Solution and each time you get a refill. There may be new information. This information does not take the place of talking with your doctor about your medical condition or your treatment.

What is XOPENEX Inhalation Solution?

XOPENEX Inhalation Solution is an inhaled prescription medicine used for the treatment or prevention of bronchospasm in people 6 years of age and older.

XOPENEX Inhalation Solution has not been shown to be safe and effective in children younger than 6 years of age.

XOPENEX Inhalation Solution is supplied in 3 mL unit-dose vials in three different strengths of levalbulterol (0.31 mg, 0.63 mg, 1.25 mg). The vials do not require dilution before use.

Who should not use XOPENEX Inhalation Solution?

Do not use XOPENEX Inhalation Solution if you are allergic to levalbuterol, racemic albuterol, or any of the ingredients in XOPENEX. See the end of this leaflet for a complete list of ingredients in XOPENEX Inhalation Solution.

What should I tell my doctor before using XOPENEX Inhalation Solution?

Before you use XOPENEX Inhalation Solution, tell your doctor if you have:

- had an allergic reaction to levalbuterol or racemic albuterol
- heart problems
- high blood pressure
- seizures
- diabetes
- thyroid problems
- any other medical conditions
- are pregnant or planning to become pregnant. It is not known if XOPENEX Inhalation Solution will harm your unborn baby. Talk to your doctor if you are pregnant or plan to become pregnant.
- are breastfeeding or plan to breastfeed. It is not known if XOPENEX Inhalation Solution passes into your breast milk. You and your doctor should decide if you will use XOPENEX Inhalation Solution or breastfeed. You should not do both.

Tell your doctor about all the medicines you take including prescription and over-the-counter medicines, vitamins, and herbal supplements. XOPENEX Inhalation Solution may affect the way other medicines work, and other medicines may affect how XOPENEX Inhalation Solution works.

Especially tell your doctor if you take:

- other asthma medicines
- heart medicines
- medicines that increase urination (diuretics)
- antidepressants
- medicine to treat chronic obstructive pulmonary disease (COPD)

Ask your doctor if you are not sure if any of your medicines are the kinds listed above.

Know the medicines you take. Keep a list of them and show it to your doctor and pharmacist when you get a new medicine.

How should I use XOPENEX Inhalation Solution?

- Read the step-by-step Instructions for Using XOPENEX Inhalation Solution at the end of this leaflet.
- Use XOPENEX Inhalation Solution exactly as your doctor tells you to. Do not change your dose without talking to your doctor first.
- Your doctor will tell you how many times and when to use your XOPENEX Inhalation Solution.
- An adult should help a child use XOPENEX Inhalation Solution.
- Do not use your XOPENEX Inhalation Solution more often than your doctor tells you to.
- Get medical help right away if XOPENEX Inhalation Solution:
  - does not work as well for your asthma symptoms or
  - your asthma symptoms get worse or
  - you need to use your XOPENEX Inhalation Solution more often than usual
- If you also use another medicine by inhalation, you should ask your doctor for instructions on when to use it while you are also using XOPENEX Inhalation Solution.
- Do not mix XOPENEX Inhalation Solution with other medicines in your nebulizer.
- Only use XOPENEX Inhalation Solution if it is colorless. Throw away the XOPENEX Inhalation Solution vial if the liquid medicine is not colorless.
- Do not use XOPENEX Inhalation Solution after the expiration date on the vial.

What are the possible side effects of XOPENEX Inhalation Solution?

XOPENEX Inhalation Solution can cause serious side effects including:

- sudden shortness of breath (bronchospasm). Sudden shortness of breath can happen right away after using XOPENEX Inhalation Solution.
- worsening asthma
- heart problems
- death. If you use too much XOPENEX Inhalation Solution you can have heart or lung problems that can lead to death.
- serious allergic reactions. Call your doctor and stop using XOPENEX Inhalation Solution right away if you have any symptoms of an allergic reaction such as:
  - swelling of the face, throat or tongue
  - hives
  - rash
  - breathing problems
- low potassium levels in your blood

Call your doctor or go to the nearest hospital emergency room right away if you have any of the serious side effects listed above or if you have worsening lung symptoms.

The most common side effects of XOPENEX Inhalation Solution include:

- palpitations
- chest pain
- fast heart rate
- headache
- dizziness
- tremor
- nervousness

Tell your doctor if you have any side effects that bother you or that do not go away.

These are not all the possible side effects of XOPENEX Inhalation Solution. For more information, ask your doctor or pharmacist.

Call your doctor for medical advice about side effects. You may report side effects to FDA at 1-800-FDA-1088.

How should I store XOPENEX Inhalation Solution?

- Store unopened XOPENEX Inhalation Solution vials in the protective foil pouch they come in between 68°F to 77°F (20°C to 25°C).
- Keep XOPENEX Inhalation Solution away from light and heat.
- When a XOPENEX Inhalation Solution foil pouch is opened, use the vials within 2 weeks.
- When XOPENEX Inhalation Solution vials are removed from the foil pouch, use them right away or within 1 week.

Keep XOPENEX Inhalation Solution and all medicines out of the reach of children.

General information about the safe and effective use of XOPENEX Inhalation Solution.

Medicines are sometimes prescribed for purposes other than those listed in a Patient Information leaflet. Do not use XOPENEX Inhalation Solution for a condition for which it was not prescribed. Do not give XOPENEX Inhalation Solution to other people, even if they have the same symptoms that you have. It may harm them.

This Patient Information leaflet summarizes the most important information about XOPENEX Inhalation Solution. If you would like more information, talk with your doctor. You can ask your pharmacist or doctor for information about XOPENEX Inhalation Solution that is written for health professionals.

There is a pregnancy exposure registry that monitors pregnancy outcomes in women exposed to asthma medication, including XOPENEX, during pregnancy. To enroll in the Asthma & Pregnancy Study or for more information about the registry, call 1-877-311-8972 or visit www.mothertobaby.org/ongoing-study/asthma.

For customer service, call 1-800-932-5676.

To report adverse events, call 1-800-932-5676.

For medical information, call 1-800-932-5676.

What are the ingredients in XOPENEX Inhalation Solution?

Active ingredient: levalbuterol hydrochloride

Inactive ingredients: sodium chloride, sulfuric acid, water and nitrogen

Instructions for Using XOPENEX Inhalation Solution

XOPENEX Inhalation Solution vial (see Figure A):

Figure A

Using your XOPENEX Inhalation Solution:

Read the following Steps before using your XOPENEX Inhalation Solution. If you have any questions, ask your doctor or pharmacist.

Step 1. Open the foil pouch by tearing the notched edge along the seam of the pouch (See Figure B). Remove 1 vial to be used right away. Keep the rest of the unused vials in the foil pouch to protect them from light and heat.

Figure B

Step 2. Hold the vial in your hands. Make sure your thumb and finger cover the twist-off tabs below the X-top (See Figure C).

Figure C

Step 3. While holding the top firmly between your thumb and finger, twist the body of the vial to open the vial (See Figure C).

Step 4. Throw away the top of the vial and squeeze the entire contents of the vial into the nebulizer reservoir (See Figure D).

Figure D

Step 5. Connect the nebulizer reservoir to the mouthpiece (See Figure E.1) or face mask (See Figure E.2).

Figure E.1

Figure E.2

Step 6. Connect the nebulizer to the compressor (See Figure F).

Figure F

Step 7. Sit in a comfortable, upright position. Place the mouthpiece in your mouth (See Figure G.1) or put on your face mask (See Figure G.2). Turn on the compressor.

Figure G.1

Figure G.2

Step 8. Breathe as calmly, deeply, and evenly as possible until no more mist is seen in the nebulizer reservoir. Your treatment will take about 5 to 15 minutes. When you do not see any mist in the nebulizer reservoir, your treatment is finished.

Step 9. Clean and store your nebulizer. See the manufacturer's instructions that come with your nebulizer for how to clean and store your nebulizer.

This Patient Information and Instructions for Use have been approved by the U.S. Food and Drug Administration.

AKORN
Distributed by: Akorn, Inc.
Lake Forest, IL 60045

Manufactured for: Oak Pharmaceuticals, Inc.

For customer service, call 1-800-932-5676.
To report adverse events, call 1-800-932-5676.
For medical information, call 1-800-932-5676.

Xopenex is a registered trademark of Sunovion Pharmaceuticals Inc. and is used under license.

XP00N December 2018
AKNX024-642R01

Principal Display Panel Text for Pouch Label:

Xopenex® NDC 17478-172-12

(levalbuterol HCl)

Inhalation Solution 0.31 mg/3 mL* *Potency expressed as levalbuterol

Principal Display Panel Text for Carton Label:

NDC 17478-172-24

0.31 mg/3 mL

Xopenex®

(levalbuterol HCl) *Potency expressed as levalbuterol

Inhalation Solution For Oral Inhalation Only. Sterile Unit-Dose Vial

0.31 mg/3 mL* 24 x 3 mL Sterile Unit-Dose Vials

Rx only

Akorn Logo

Principal Display Panel Text for Pouch Label:

Xopenex® NDC 17478-173-12

(levalbuterol HCl)

Inhalation Solution 0.63 mg/3 mL* *Potency expressed as levalbuterol

Principal Display Panel Text for Carton Label:

NDC 17478-173-24

0.63 mg/3 mL

Xopenex®

(levalbuterol HCl) *Potency expressed as levalbuterol

Inhalation Solution For Oral Inhalation Only. Sterile Unit-Dose Vial

0.63 mg/3 mL* 24 x 3 mL Sterile Unit-Dose Vials

Rx only

Akorn Logo

Principal Display Panel Text for Pouch Label:

Xopenex® NDC 17478-174-12

(levalbuterol HCl)

Inhalation Solution 1.25 mg/3 mL* *Potency expressed as levalbuterol

Principal Display Panel Text for Carton Label:

NDC 17478-174-24

1.25 mg/3 mL

Xopenex®

(levalbuterol HCl) *Potency expressed as levalbuterol

Inhalation Solution For Oral Inhalation Only. Sterile Unit-Dose Vial

1.25 mg/3 mL* 24 x 3 mL Sterile Unit-Dose Vials

Rx only

Akorn Logo